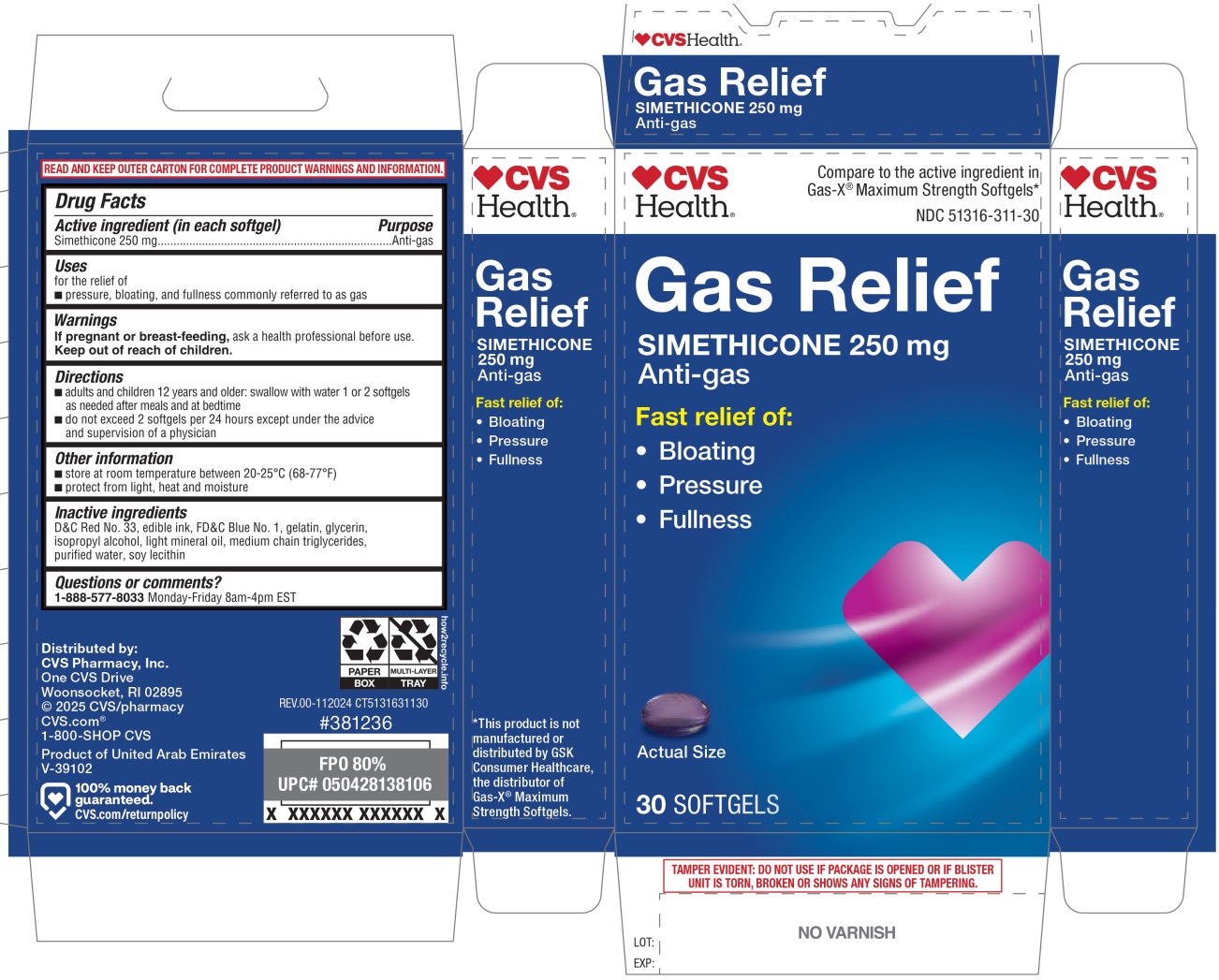 DRUG LABEL: CVS Health Gas Relief SOFTGEL
NDC: 51316-311 | Form: CAPSULE, LIQUID FILLED
Manufacturer: CVS Pharmacy, Inc
Category: otc | Type: HUMAN OTC DRUG LABEL
Date: 20250822

ACTIVE INGREDIENTS: DIMETHICONE, UNSPECIFIED 250 mg/1 1
INACTIVE INGREDIENTS: D&C RED NO. 33; FD&C BLUE NO. 1; GELATIN, UNSPECIFIED; GLYCERIN; ISOPROPYL ALCOHOL; LIGHT MINERAL OIL; MEDIUM-CHAIN TRIGLYCERIDES; WATER; SOYBEAN LECITHIN

CVS Health® Gas Relief SOFTGEL

Active ingredient (in each softgel)

Simethicone 250 mg

Purpose

Anti-gas

Uses

for the relief of
• pressure, bloating, and fullness commonly referred to as gas

Warnings

If pregnant or breast-feeding, ask a health professional before use.

Keep out of reach of children.

Directions

• adults and children 12 years and older: swallow with water 1 or 2 softgels as needed after meals and at bedtime
• do not exceed 2 softgels per 24 hours except under the advice and supervision of a physician

Other information

• store at room temperature between 20-25°C (68-77°F)
• protect from light, heat and moisture

Inactive ingredients

D&C Red No. 33, edible ink, FD&C Blue No. 1, gelatin, glycerin, isopropyl alcohol, light mineral oil, medium chain triglycerides, purified water, soy lecithin

Questions or comments?

1-888-577-8033 Monday-Friday 8am-4pm EST

Compare to the active ingredient in Gas-X® Maximum Strength Softgels*

Fast relief of:
• Bloating
• Pressure
• Fullness

READ AND KEEP OUTER CARTON FOR COMPLETE PRODUCT WARNINGS AND INFORMATION.

Distributed by:
CVS Pharmacy, Inc.
One CVS Drive
Woonsocket, RI 02895
© 2025 CVS/pharmacy
CVS.com®
1-800-SHOP CVS

Product of United Arab Emirates
V-39102

100% money back guaranteed.
CVS.com/returnpolicy

*This product is not manufactured or distributed by GSK Consumer Healthcare, the distributor of Gas-X® Maximum Strength Softgels.

TAMPER EVIDENT: DO NOT USE IF PACKAGE IS OPENED OR IF BLISTER UNIT IS TORN, BROKEN OR SHOWS ANY SIGNS OF TAMPERING.